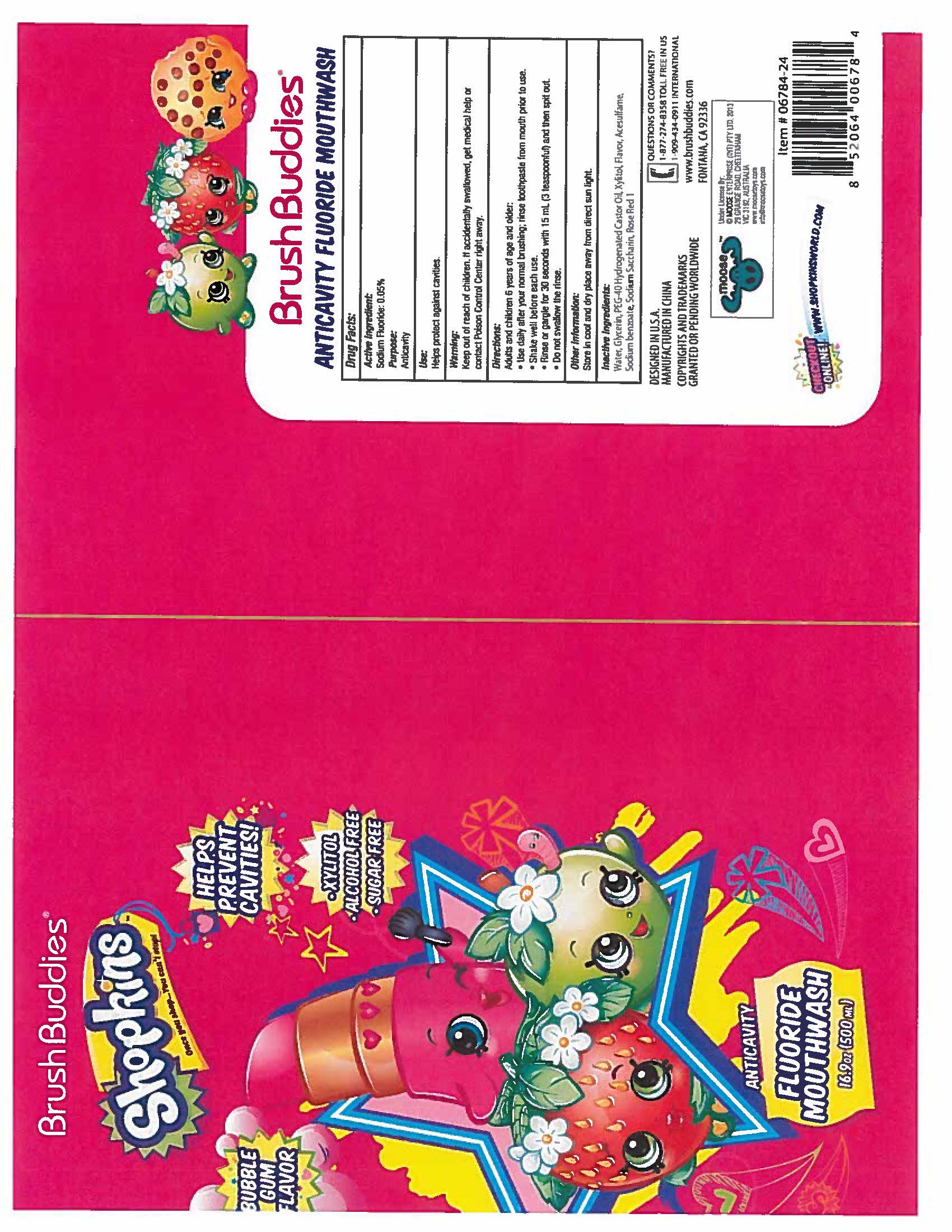 DRUG LABEL: Brushbuddies Shopkins Anticavity Fluoride
NDC: 70108-502 | Form: MOUTHWASH
Manufacturer: Ashtel Studio Inc
Category: otc | Type: HUMAN OTC DRUG LABEL
Date: 20161203

ACTIVE INGREDIENTS: SODIUM FLUORIDE 0.0225 g/100 g
INACTIVE INGREDIENTS: WATER; GLYCERIN; XYLITOL; ACESULFAME; SODIUM BENZOATE; ROSE BENGAL AT; SACCHARIN SODIUM

Active Ingredient

Sodium Fluoride 0.05%

Purpose:

Anticavity

Uses:

Helps protect against cavities

Warnings:

If you accidentally swallow more than used for brushing, seek professional help or contact a Poison Control Center immediately

Keep out of reach of children

Directions:

- Adults and children 6 years and older:
- Use daily after your normal brush
- Shake well before each use
- Rinse or gargle for 30 seconds with 15 mL (3 teaspoonful) and then spit out
- Supervise children's brushing untill good habits are established.
- Do not Swallow the rinse

Other Information

Store in cool and dry place away from direct sun light

Inactive Ingredients:

Water, Glycerin, PEG-40 Hydrogenated Castor Oil, Xylitor, Flavor, Acesulfame, Sodium Benzoate, Saccharin Sodium, Rose Red 1